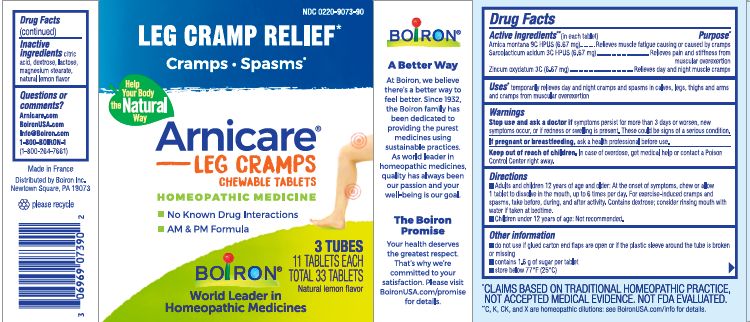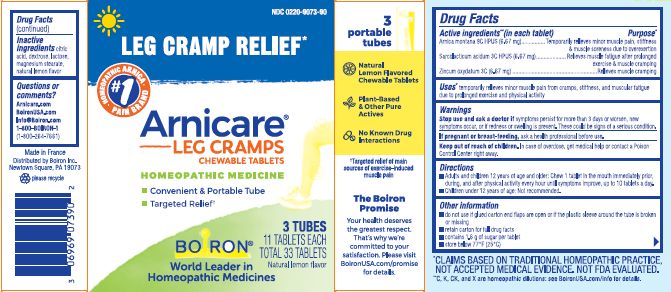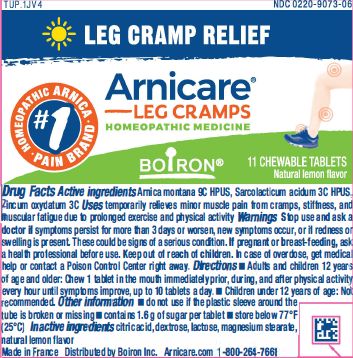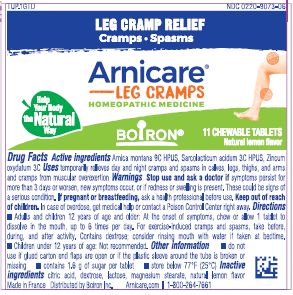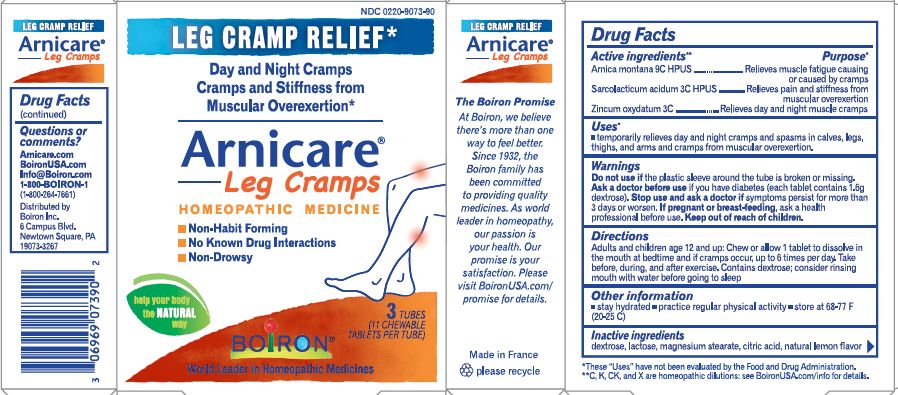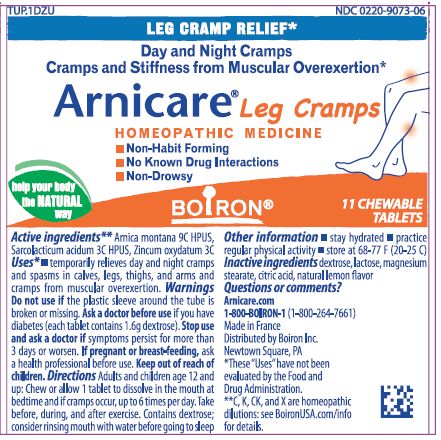 DRUG LABEL: Arnicare Leg Cramps
NDC: 0220-9073 | Form: TABLET
Manufacturer: Boiron
Category: homeopathic | Type: HUMAN OTC DRUG LABEL
Date: 20240201

ACTIVE INGREDIENTS: ARNICA MONTANA 9 [hp_C]/1 1; ZINC OXIDE 3 [hp_C]/1 1; LACTIC ACID, L- 3 [hp_C]/1 1
INACTIVE INGREDIENTS: WATER; CITRIC ACID MONOHYDRATE; MAGNESIUM STEARATE; DEXTROSE MONOHYDRATE; LEMON; LACTOSE, UNSPECIFIED FORM

Arnicare Leg Cramps

Active Ingredients**

Arnica montana 9C HPUS (6.67 mg)

Sarcolacticum acidum 3C HPUS (6.67 mg)

Zincum oxydatum 3C (6.67 mg)

Purpose*

Arnica montana 9C HPUS ... Temporarily relieves minor pain, stiffness & muscle soreness due to overexertion

Sarcolacticum acidum 3C HPUS ... Relieves muscle fatigue after prolonged exercise & muscle cramping

Zincum oxydatum 3C ... Relieves muscle cramping

Uses*

temporarily relieves minor muscle pain from cramps, stiffness, and muscular fatigue due to prolonged exercise and physical activity

Stop use and ask a doctor if symptoms persist for more than 3 days or worsen, new symptoms occur, or if redness or swelling is present. These could be signs of a serious condition.

PREGNANCY OR BREAST FEEDING

If pregnant or breast-feeding, ask a health professional before use.

Keep out of reach of children. In case of overdose, get medical help or contact a Poison Control Center right away.

Directions

Adults and children 12 years of age and older: Chew 1 tablet in the mouth immediately prior, during, and after physical activity every hour until symptoms improve, up to 10 tablets a day.

Children under 12 years of age: Not recommended.

do not use if glued carton end flaps are open or if the plastic sleeve around the tube is broken or missing

retain carton for full drug facts

contains 1.6 g of sugar per tablet

store below 77° F (25°C)

INACTIVE INGREDIENT

citric acide, dextrose, lactose, magnesium stearate, natural lemon flavor

3 Tubes 11 Tablets Each Total 33 Tablets

Natural lemon flavor

No Known Drug Interactions

Leg Cramp Relief*

Cramps Spasms*

Target Relief of main sources of exercise-induced muscle pain

*CLAIMS BASED ON TRADITIONAL HOMEOPATHIC PRACTICE, NOT ACCEPTED MEDICAL EVIDENCE. NOT FDA EVALUATED.
*C,K,CK, and X are homeopathic dilutions: see BoironUSA.com/info for details.

QUESTIONS

Quesions or comments?

Arnicare.com

BoironUSA.com

Info@Boiron.com

1-800-BOIRON-1

(1-800-264-7661)

Made in France

Distributed by: Boiron Inc.

Newtown Square, PA 19073-3267